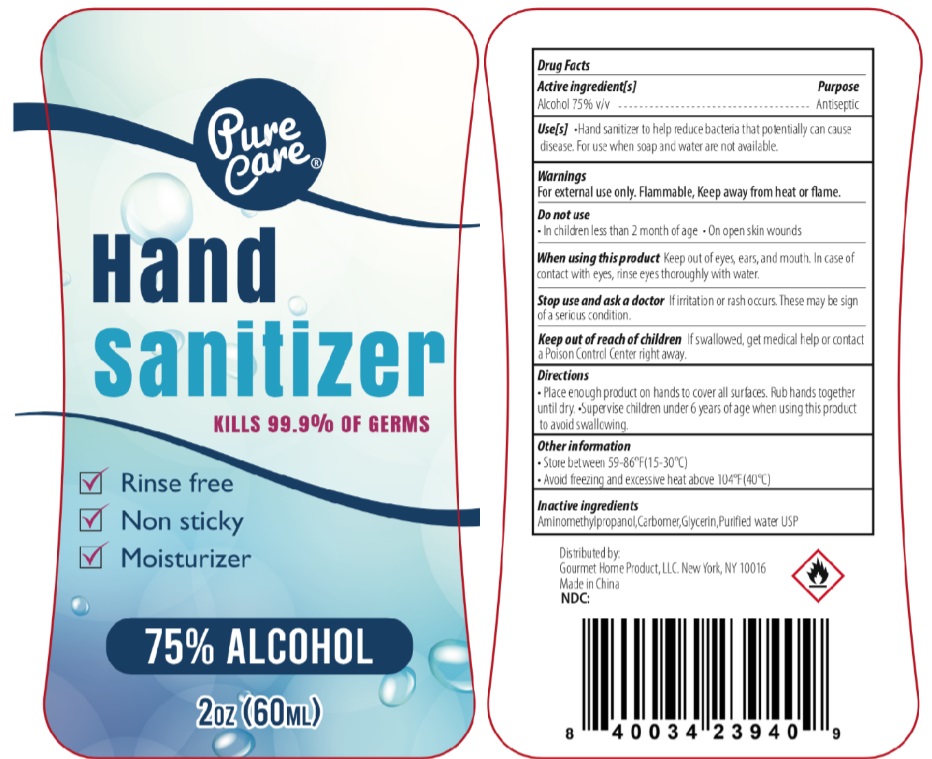 DRUG LABEL: Pure care hand sanitizer
NDC: 73928-004 | Form: GEL
Manufacturer: KINGKEY MBC LIFE TECHNOLOGY GROUP CO., LTD
Category: otc | Type: HUMAN OTC DRUG LABEL
Date: 20251007

ACTIVE INGREDIENTS: ALCOHOL 75 mL/100 mL
INACTIVE INGREDIENTS: WATER; GLYCERIN; CARBOMER HOMOPOLYMER TYPE C (ALLYL PENTAERYTHRITOL CROSSLINKED); AMINOMETHYLPROPANOL

Active Ingredient

Alcohol 75% v/v.

Purpose

Antiseptic

Uses

Hand Sanitizer to help reduce bacteria that potentially can cause disease. For use when soap and water are not available.

Warnings

For external use only. Flammable. Keep away from heat or flame.

Do not use

- in children less than 2 months of age
- on open skin wounds

When using this productkeep out of eyes, ears, and mouth. In case of contact with eyes, rinse eyes thoroughly with water.
Stop use and ask a doctor ifirritation or rash occurs. These may be signs of a serious condition.

Keep out of reach of children.If swallowed, get medical help or contact a Poison Control Center right away.

Directions

- Place enough product on hands to cover all surfaces. Rub hands together until dry.
- Supervise children under 6 years of age when using this product to avoid swallowing.

Other information

- Store between 59-86^0F (15-30^0C)
- Avoid freezing and excecssive heat above 104^0F (40^0C)